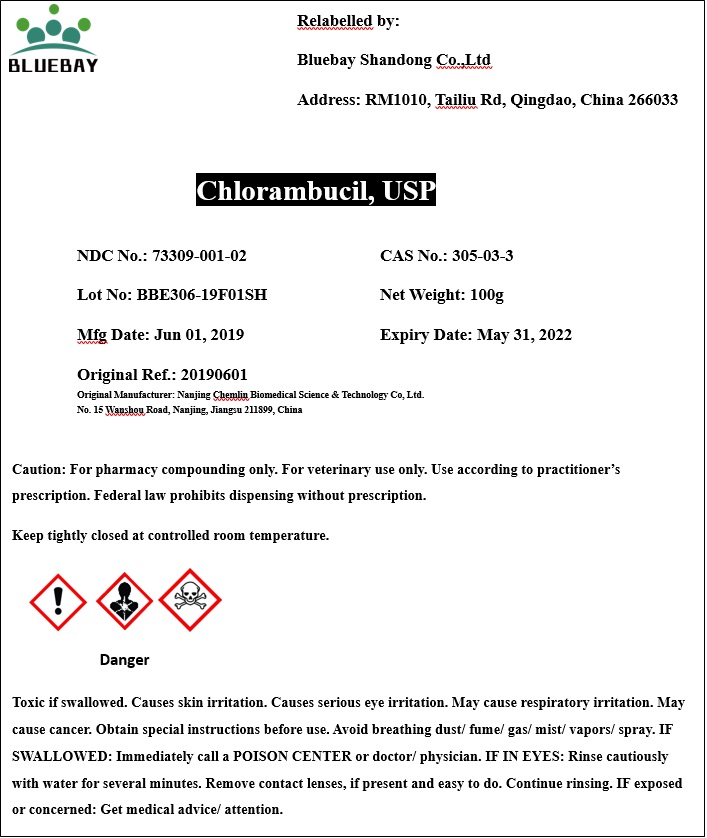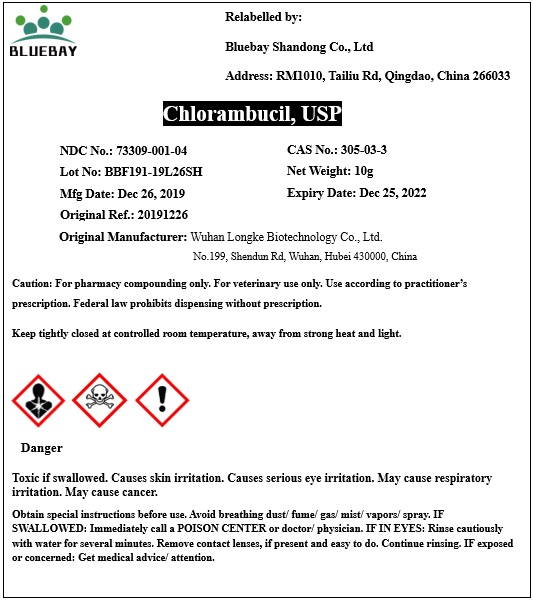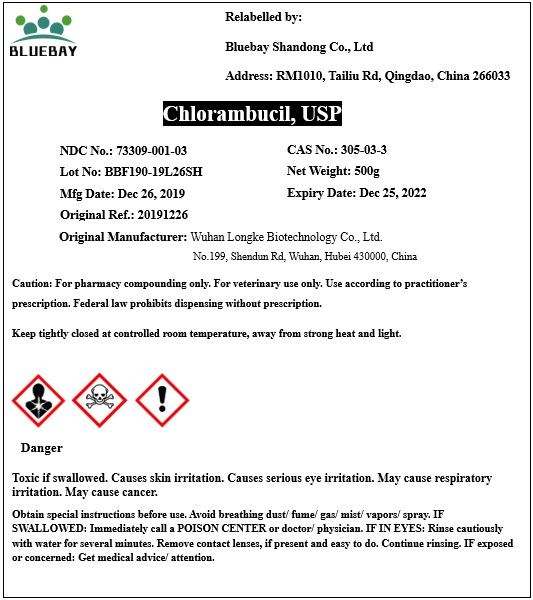 DRUG LABEL: Chlorambucil
NDC: 73309-001 | Form: POWDER
Manufacturer: BLUEBAY SHANDONG CO.,LTD
Category: other | Type: BULK INGREDIENT
Date: 20200416

ACTIVE INGREDIENTS: CHLORAMBUCIL 1 g/1 g

Chlorambucil